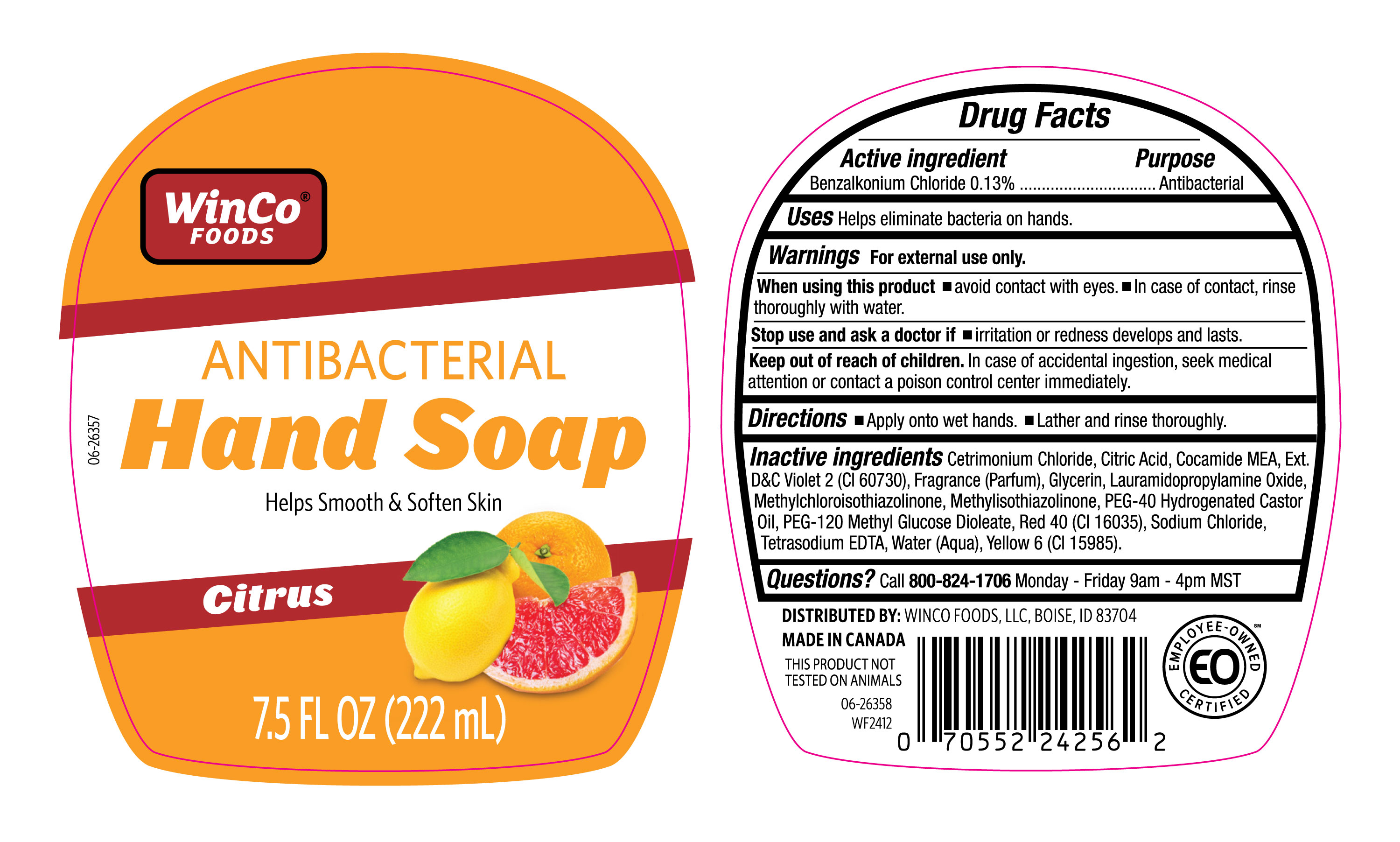 DRUG LABEL: WINCO CITRUS LHS
NDC: 67091-111 | Form: LIQUID
Manufacturer: WINCO FOODS, LLC
Category: otc | Type: HUMAN OTC DRUG LABEL
Date: 20250319

ACTIVE INGREDIENTS: BENZALKONIUM CHLORIDE 130 mg/100 mL
INACTIVE INGREDIENTS: CETRIMONIUM CHLORIDE; CITRIC ACID; WATER; PEG-120 METHYL GLUCOSE DIOLEATE; RED 40; EXT. VIOLET 2; FRAGRANCE CLEAN ORC0600327; METHYLISOTHIAZOLINONE; TETRASODIUM EDTA; YELLOW 6; METHYLCHLOROISOTHIAZOLINONE; COCAMIDE MEA; GLYCERIN; PEG-40 HYDROGENATED CASTOR OIL; SODIUM CHLORIDE; LAURAMIDOPROPYLAMINE OXIDE

NDC-67091-111, WINCO CITRUS ANTIBAC LHS.

Active Ingredient

Benzalkonium Chloride 0.13%

Purpose

Antibacterial

Uses

Helps eliminate bacteria on hands.

Warnings

For external use only.

When using this product

- Avoid contact with eyes.
- In case of contact, rinse thorougly with water.

Stop use and ask a doctor if

- Irritation or redness develops and lasts.

Keep out of reach of children.

In case of accidental ingestion, seek medical attention or contact a poison control center immediately.

Directions

- Apply onto we hands.
- Lather and rinse thoroughly.

Inactive ingredients

Centrimonium Chloride, CitricAcid, Cocamide MEA, Ext. D&C Violet 2 (CI 60730), Fragrance (Parfum), Glycerin, Lauramidopropylamine Oxide, Methylchloroisothiazolinone, PEG-40 Hydrogenated Castor Oil, PEG-120 Methyl Glucose Dioleate, Red 40 (CI 16035), Sodium Chloride, Tetrasodium EDTA, Water (Aqua), Yello 6 (CI 15985).

Questions?

Call 800-824-1706 Monday - Friday 9am - 4pm MST